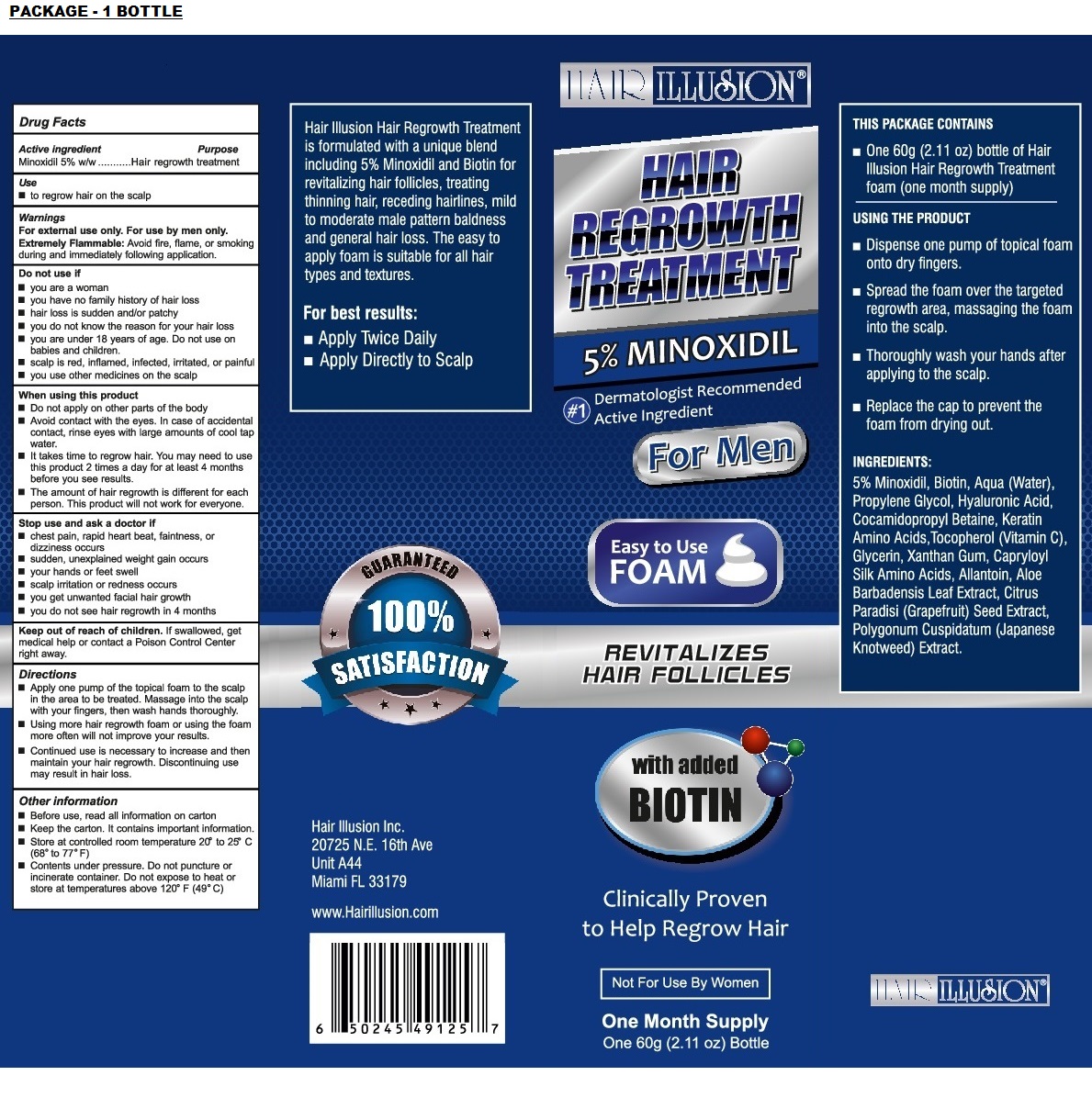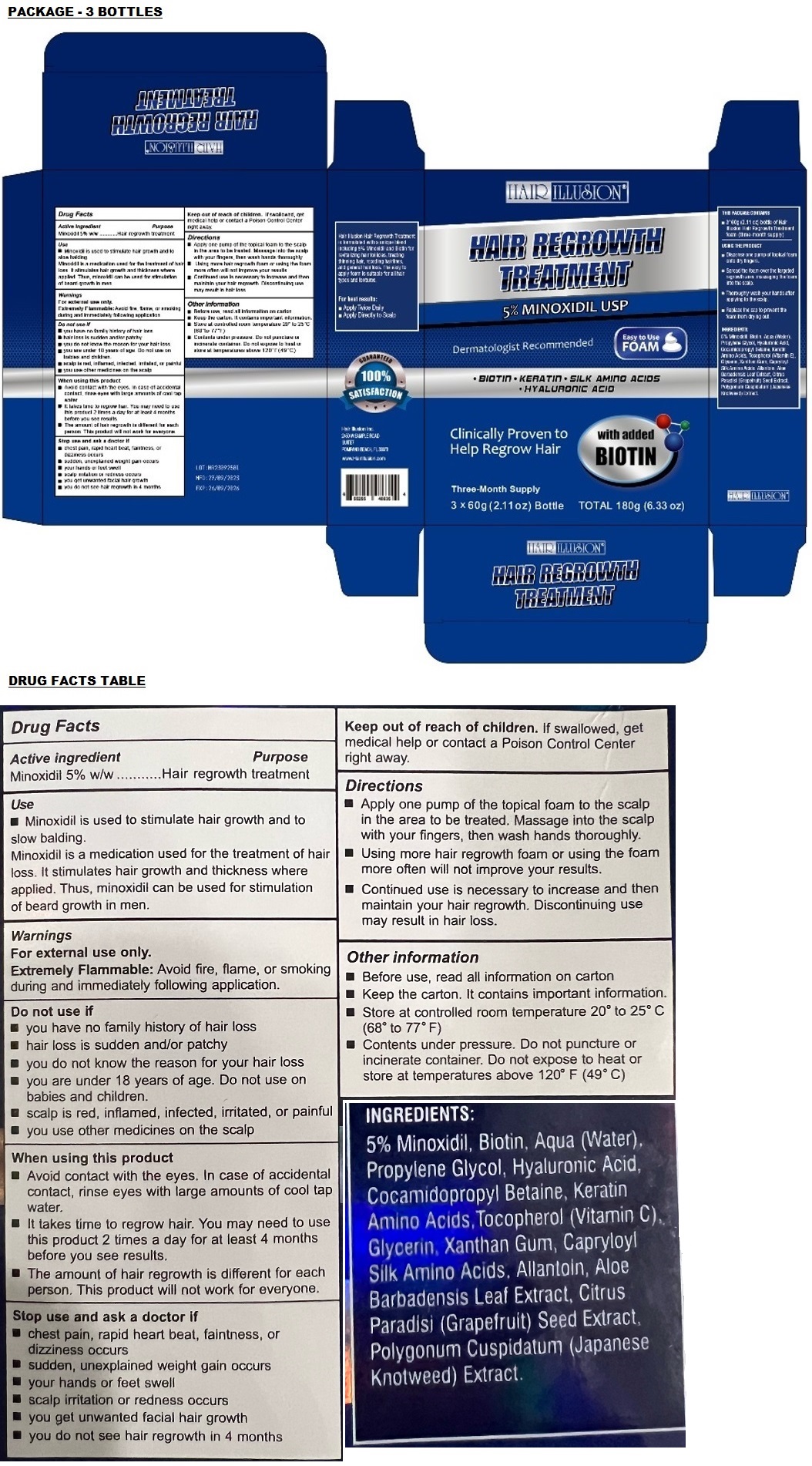 DRUG LABEL: Hair Illusion 5% Minoxidil Foam
NDC: 83572-999 | Form: AEROSOL, FOAM
Manufacturer: Hair Illusion
Category: otc | Type: HUMAN OTC DRUG LABEL
Date: 20231103

ACTIVE INGREDIENTS: MINOXIDIL 5 g/100 g
INACTIVE INGREDIENTS: BIOTIN; WATER; PROPYLENE GLYCOL; HYALURONIC ACID; COCAMIDOPROPYL BETAINE; HAIR KERATIN AMINO ACIDS; TOCOPHEROL; GLYCERIN; XANTHAN GUM; AMINO ACIDS, SILK; ALLANTOIN; ALOE VERA LEAF; CITRUS PARADISI SEED; REYNOUTRIA JAPONICA WHOLE

HAIR ILLUSION 5% MINOXIDIL FOAM

Active ingredient

Minoxidil 5% w/w

Purpose

Hair regrowth treatment

Use

• Minoxidil is used to stimulate hair growth and to slow balding.
Minoxidil is a medication used for the treatment of hair loss. It stimulates hair growth and thickness where applied. Thus, minoxidil can be used for stimulation of beard growth in men.

Warnings

For external use only.

Extremely Flammable: Avoid fire, flame, or smoking during and immediately following application.

Do not use if
• you have no family history of hair loss
• hair loss is sudden and/or patchy
• you do not know the reason for your hair loss
• you are under 18 years of age. Do not use on babies and children.
• scalp is red, inflamed, infected, irritated, or painful
• you use other medicines on the scalp

When using this product
• Avoid contact with the eyes. In case of accidental contact, rinse eyes with large amounts of cool tap water.
• It takes time to regrow hair. You may need to use this product 2 times a day for at least 4 months before you see results.
• The amount of hair regrowth is different for each person. This product will not work for everyone.

Stop use and ask a doctor if
• chest pain, rapid heart beat, faintness, or dizziness occurs
• sudden, unexplained weight gain occurs
• your hands or feet swell
• scalp irritation or redness occurs
• you get unwanted facial hair growth
• you do not see hair regrowth in 4 months

Keep out of reach of children. If swallowed, get medical help or contact a Poison Control Center right away.

Directions

• Apply one pump of the topical foam to the scalp in the area to be treated. Massage into the scalp with your fingers, then wash hands thoroughly.
• Using more hair regrowth foam or using the foam more often will not improve your results.
• Continued use is necessary to increase and then maintain your hair regrowth. Discontinuing use may result in hair loss.

USING THE PRODUCT
• Dispense on pump of topical foam onto dry fingers.
• Spread the foam over the targeted regrowth area, massaging the foam into the scalp.
• Thoroughly wash your hands after applying to the scalp.
• Replace the cap to prevent the foam from drying out.

Other information

• Before use, read all information on carton
• Keep the carton. It contains important information.
• Store at controlled room temperature 20° to 25° C (68° to 77° F)
• Contents under pressure. Do not puncture or incinerate container. Do not expose to heat or store at temperatures above 120° F (49° C)

INGREDIENTS:

5% Minoxidil, Biotin, Aqua (Water), Propylene Glycol, Hyaluronic Acid, Cocamidopropyl Betaine, Keratin Amino Acids, Tocopherol (Vitamin C), Glycerin, Xanthan Gum, Capryloyl Silk Amino Acids, Allantoin, Aloe Barbadensis Leaf Extract, Citrus Paradisi (Grapefruit) Seed Extract, Polygonum Cuspidatum (Japanese Knotweed) Extract.

HAIR REGROWTH TREATMENT

Dermatologist Recommended Active Ingredient

Easy to use FOAM

REVITALIZES HAIR FOLLICLES

with added BIOTIN

Clinically Proven to Help Regrow Hair

Not For Use By Women

One Month Supply

Three-Month Supply

Hair Illusion Hair Regrowth Treatment is formulated with a unique blend including 5% Minoxidil and Biotin for revitalizing hair follicles, treating thinning hair, receding hairlines, mild to moderate male pattern baldness and general hair loss. The easy to apply foam is suitable for all hair types and textures.

For best results:
• Apply Twice Daily
• Apply Directly to Scalp

100% SATISFACTION GUARANTEED

Hair Illusion Inc.
20725 N.E. 16th Ave
Unit A44
Miami FL 33179

www.Hairillusion.com